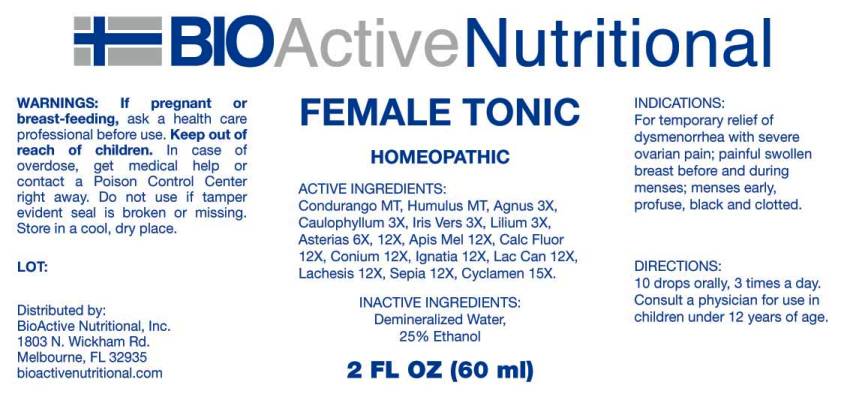 DRUG LABEL: Female Tonic
NDC: 43857-0333 | Form: LIQUID
Manufacturer: BioActive Nutritional, Inc.
Category: homeopathic | Type: HUMAN OTC DRUG LABEL
Date: 20160927

ACTIVE INGREDIENTS: MARSDENIA CONDURANGO BARK 1 [hp_X]/1 mL; HOPS 1 [hp_X]/1 mL; CHASTE TREE 3 [hp_X]/1 mL; CAULOPHYLLUM THALICTROIDES ROOT 3 [hp_X]/1 mL; IRIS VERSICOLOR ROOT 3 [hp_X]/1 mL; LILIUM LANCIFOLIUM WHOLE FLOWERING 3 [hp_X]/1 mL; ASTERIAS RUBENS 6 [hp_X]/1 mL; APIS MELLIFERA 12 [hp_X]/1 mL; CALCIUM FLUORIDE 12 [hp_X]/1 mL; CONIUM MACULATUM FLOWERING TOP 12 [hp_X]/1 mL; STRYCHNOS IGNATII SEED 12 [hp_X]/1 mL; CANIS LUPUS FAMILIARIS MILK 12 [hp_X]/1 mL; LACHESIS MUTA VENOM 12 [hp_X]/1 mL; SEPIA OFFICINALIS JUICE 12 [hp_X]/1 mL; CYCLAMEN PURPURASCENS TUBER 15 [hp_X]/1 mL
INACTIVE INGREDIENTS: WATER; ALCOHOL

Drug Facts:

ACTIVE INGREDIENTS:

Condurango 1X, Humulus Lupulus 1X, Agnus Castus 3X, Caulophyllum Thalictroides 3X, Iris Versicolor 3X, Lilium Tigrinum 3X, Asterias Rubens 6X, 12X, Apis Mellifica 12X, Calcarea Fluorica 12X, Conium Maculatum 12X, Ignatia Amara 12X, Lac Caninum 12X, Lachesis Mutus 12X, Sepia 12X, Cyclamen Europaeum 15X.

INDICATIONS:

For temporary relief of dysmenorrhea with severe ovarian pain; painful swollen breast before and during menses; menses early, profuse, black and clotted.

WARNINGS:

If pregnant or breast-feeding, ask a health care professional before use.

Keep out of reach of children. In case of overdose, get medical help or contact a Poison Control Center right away.

Do not use if tamper evident seal is broken or missing.

Store in cool, dry place.

Keep out of reach of children. In case of overdose, get medical help or contact a Poison Control Center right away.

DIRECTIONS:

10 drops orally, 3 times a day. Consult a physician for use in children under 12 years of age.

INDICATIONS:

For temporary relief of dysmenorrhea with severe ovarian pain; painful swollen breast before and during menses; menses early, profuse, black and clotted.

INACTIVE INGREDIENTS:

Demineralized Water, 25% Ethanol.

QUESTIONS:

Distributed by:
BioActive Nutritional, Inc.
1803 N. Wickham Rd.
Melbourne, FL 32935
bioactivenutritional.com

PACKAGE LABEL DISPLAY:

BIOActive Nutritional

FEMALE TONIC

HOMEOPATHIC

2 FL OZ (60 ml)